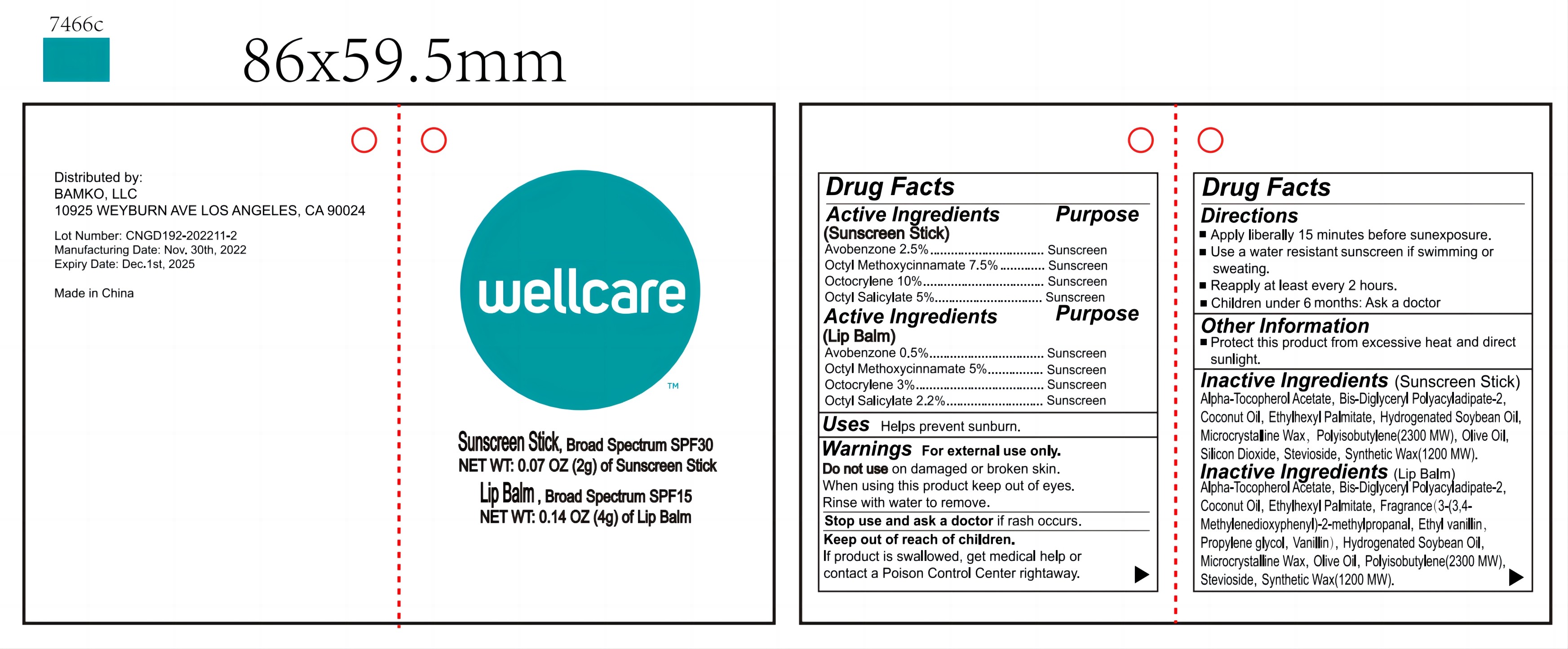 DRUG LABEL: Wellcare Sunstick
NDC: 54860-403 | Form: PASTE
Manufacturer: Shenzhen Lantern Scicence Co.,Ltd.
Category: otc | Type: HUMAN OTC DRUG LABEL
Date: 20221120

ACTIVE INGREDIENTS: OCTINOXATE 12.5 g/200 g; OCTISALATE 7.2 g/200 g; AVOBENZONE 3 g/200 g; OCTOCRYLENE 13 g/200 g
INACTIVE INGREDIENTS: VANILLIN 0.125 g/200 g; PROPYLENE GLYCOL 0.125 g/200 g; ETHYL VANILLIN 0.125 g/200 g; 3-(3,4-METHYLENEDIOXYPHENYL)-2-METHYLPROPANAL 0.125 g/200 g; STEVIOSIDE 1 g/200 g; ETHYLHEXYL PALMITATE 34.6 g/200 g; COCONUT OIL 33 g/200 g; POLYISOBUTYLENE (2300 MW) 27 g/200 g; MICROCRYSTALLINE WAX 20 g/200 g; SYNTHETIC WAX (1200 MW) 18 g/200 g; HYDROGENATED SOYBEAN OIL 16 g/200 g; OLIVE OIL 7 g/200 g; BIS-DIGLYCERYL POLYACYLADIPATE-2 5 g/200 g; SILICON DIOXIDE 2 g/200 g; ALPHA-TOCOPHEROL ACETATE 0.2 g/200 g

Wellcare Sunstick

Active Ingredient

(Sunscreen Stick)
Avobenzone 2.5mg Sunscreen
Octyl Methoxycinnamate 7.5mg Sunscreen
Octocrylene 10mg Sunscreen
OctyI Salicylate 5mg Sunscreen
(Lip Balm)
Avobenzone 0. 5mg.
Octyl Methoxycinnamate 5mg Sunscreen
Octocrylene 3 Sunscreen
OctyI Salicylate 2.2mg Sunscreen

Inactive ingredients

Ethylhexyl Palmitate, Coconut Oil, Polyisobutylene(2300 MW), Microcrystalline Wax, Synthetic Wax(1200 MW), Hydrogenated Soybean Oil, Olive Oil, Bis-Diglyceryl Polyacyladipate-2, Silicon Dioxide, Stevioside, "3-(3,4-Methylenedioxyphenyl)-2-methylpropanal, Ethyl vanillin, Vanillin, Propylene glycol", Alpha-Tocopherol Acetate

Directions

Apply liberally 15 minutes before sunexposure.
Use a water resistant sunscreen if swimming or sweating.
Reapply at least every 2 hours.
Children under 6 months: Ask a docto

When using this product

Keep out of reach of children.
If product is swallowed, get medical help or contact a Poison Control Center rightaway

Purpose

Sunscreen

Stop use and ask a doctor

if rash occurs.

Do not use

On damaged or broken skin.
When using this product keep out of eyes.
Rinse with water to remove

Other information

Protect this product from excessive heat and direct sunlight

use

Helps prevent sunburn.

warnings

For external use only.

Keep out of reach of children

If product is swallowed, get medical help or contact a Poison Control Center rightaway.

usage

Apply liberally 15 minutes before sunexposure.
Use a water resistant sunscreen if swimming or sweating.
Reapply at least every 2 hours.
Children under 6 months: Ask a docto